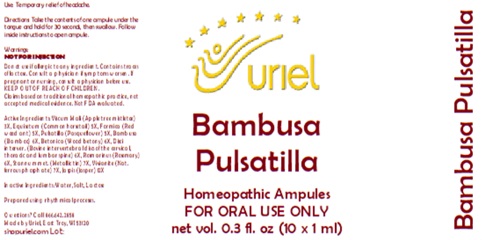 DRUG LABEL: Bambusa Pulsatilla
NDC: 48951-2014 | Form: LIQUID
Manufacturer: Uriel Pharmacy Inc.
Category: homeopathic | Type: HUMAN OTC DRUG LABEL
Date: 20251126

ACTIVE INGREDIENTS: VISCUM ALBUM FRUITING TOP 3 [hp_X]/1 mL; EQUISETUM ARVENSE TOP 5 [hp_X]/1 mL; FORMICA RUFA 5 [hp_X]/1 mL; PULSATILLA VULGARIS 5 [hp_X]/1 mL; BAMBUSA VULGARIS WHOLE 6 [hp_X]/1 mL; STACHYS OFFICINALIS 6 [hp_X]/1 mL; BOS TAURUS INTERVERTEBRAL DISC 6 [hp_X]/1 mL; ROSMARINUS OFFICINALIS FLOWERING TOP 6 [hp_X]/1 mL; TIN 7 [hp_X]/1 mL; FERROSOFERRIC PHOSPHATE 7 [hp_X]/1 mL; SILICON DIOXIDE 12 [hp_X]/1 mL
INACTIVE INGREDIENTS: WATER; SODIUM CHLORIDE; LACTOSE

Bambusa Pulsatilla

PURPOSE

Use: Temporary relief of headache.

INDICATIONS AND USAGE

FOR ORAL USE ONLY

DOSAGE AND ADMINISTRATION

Directions: Take the contents of one ampule under the tongue and hold for 30 seconds, then swallow. Follow inside instructions to open ampule.

Warnings:
NOT FOR INJECTION
Do not use if allergic to any ingredient. Contains traces of lactose. Consult a physician if symptoms worsen. If pregnant or nursing, consult a physician before use.
Claims based on traditional homeopathic practice, not accepted medical evidence. Not FDA evaluated.

KEEP OUT OF REACH OF CHILDREN.

ACTIVE INGREDIENT

Active Ingredients: Viscum Mali (Apple tree mistletoe) 3X, Equisetum (Common horsetail) 5X, Formica (Red wood ant) 5X, Pulsatilla (Pasqueflower) 5X, Bambusa (Bamboo) 6X, Betonica (Wood betony) 6X, Disci interver. (Bovine intervertebral discs of the cervical, thoracic and lumbar spine) 6X, Rosmarinus (Rosemary) 6X, Stannum met. (Metallic tin) 7X, Vivianite (Nat. ferrous phosphate) 7X, Jasper 12X

Inactive Ingredients: Water, Salt, Lactose

Prepared using rhythmical processes.

QUESTIONS

Questions? Call 866.642.2858 Made by Uriel, East Troy, WI 53120 shopuriel.com Lot: